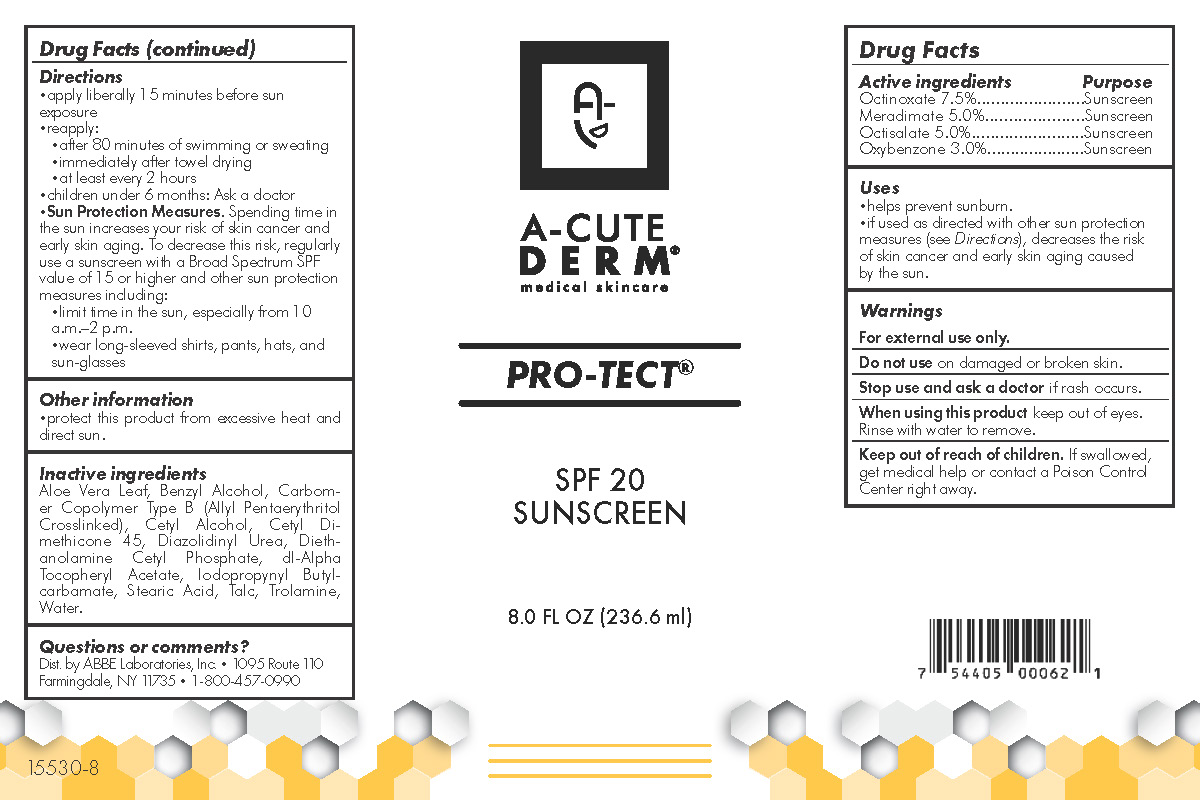 DRUG LABEL: Pro-Tect Sports Sunscreen SPF 20
NDC: 68605-8640 | Form: LOTION
Manufacturer: ABBE Laboratories, Inc.
Category: otc | Type: HUMAN OTC DRUG LABEL
Date: 20260113

ACTIVE INGREDIENTS: OCTINOXATE 75 mg/1 g; MERADIMATE 50 mg/1 g; OXYBENZONE 30 mg/1 g; OCTISALATE 50 mg/1 g
INACTIVE INGREDIENTS: ALOE VERA LEAF; BENZYL ALCOHOL; DIAZOLIDINYL UREA; CETYL ALCOHOL; CARBOMER COPOLYMER TYPE B (ALLYL PENTAERYTHRITOL CROSSLINKED); CETYL DIMETHICONE 45; DIETHANOLAMINE CETYL PHOSPHATE; .ALPHA.-TOCOPHEROL ACETATE, DL-; IODOPROPYNYL BUTYLCARBAMATE; STEARIC ACID; TALC; TROLAMINE; WATER

Active ingredients

Meradimate 5.0%

Octinoxate 7.5%

Octisalate 5.0%

Oxybenzone 3.0%

Purpose

Sunscreen

Uses

•helps prevent sunburn.
•if used as directed with other sun protection
measures (see Directions), decreases the risk
of skin cancer and early skin aging caused
by the sun.

Warnings

For external use only.
Do not use on damaged or broken skin.
Stop use and ask a doctor if rash occurs.
When using this product keep out of eyes.
Rinse with water to remove.

Keep out of reach of children. If swallowed,
get medical help or contact a Poison
Control Center right away.

Directions

•apply liberally 15 minutes before sun exposure
•reapply:
•after 80 minutes of swimming or sweating

•immediately after towel drying
•at least every 2 hours
•children under 6 months: Ask a doctor
• Sun Protection Measures. Spending
time in the sun increases your risk of skin
cancer and early skin aging. To decrease this
risk, regularly use a sunscreen with a Broad
Spectrum SPF value of 15 or higher and other
sun protection measures including:
•limit time in the sun, especially from 10a.m.–2 p.m.
•wear long-sleeved shirts, pants, hats, and sun-glasses

Other Information

•protect this product from excessive heat and direct sun.

Inactive Ingredients

Aloe Vera Leaf, Benzyl Alcohol, Carbomer Copolymer Type B (Allyl Pentaerythritol Crosslinked), Cetyl Alcohol, Cetyl Dimethicone 45, Diazolidinyl Urea, Diethanolamine Cetyl Phospate, dl-Alpha Tocopheryl Acetate, Iodopropynyl Butylcarbamate, Stearic Acid, Talc, Trolamine, Water.

Questions or Comments

Dist. by ABBE Laboratories, Inc. • 1095 Route 110
Farmingdale, NY 11735 • 1-800-457-0990

RECENT MAJOR CHANGES

Uses 12/2020

Directions 12/2020

Package Label

A-CUTE DERM ®

medical skincare

PRO-TECT

SPF 20

SUNSCREEN

8.0 FL OZ (236.6 ml)